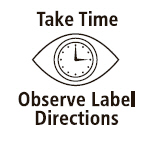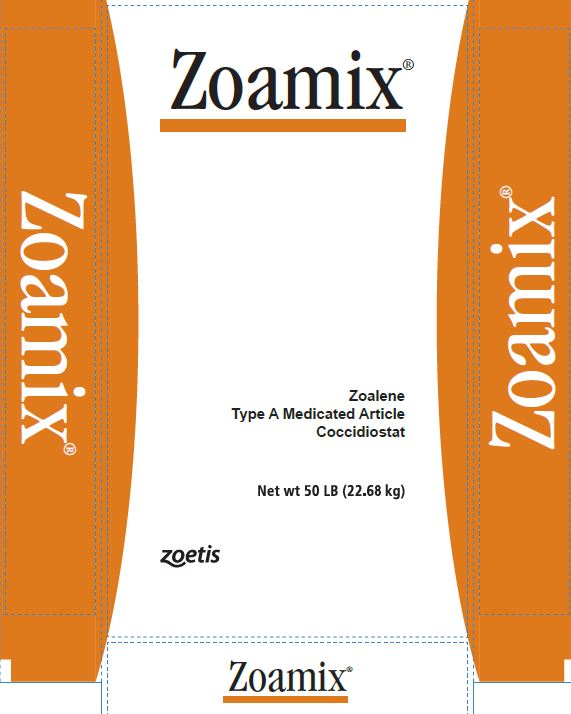 DRUG LABEL: Zoamix
NDC: 54771-1116 | Form: POWDER
Manufacturer: Zoetis Inc.
Category: animal | Type: OTC TYPE A MEDICATED ARTICLE ANIMAL DRUG LABEL
Date: 20230707

ACTIVE INGREDIENTS: DINITOLMIDE 5.67 kg/22.68 kg
INACTIVE INGREDIENTS: MINERAL OIL

Zoamix®

Zoalene
Type A Medicated Article
Coccidiostat

DESCRIPTION

Active drug ingredient
Zoalene (3,5-dinitro-o-toluamide) | 25%

Inactive ingredients
Roughage product, ground limestone, mineral oil | 75%

INDICATIONS AND USAGE

For use in preparation of feeds for chickens and turkeys only.

Livestock remedy.

Indications

Broiler Chickens: For prevention and control of coccidiosis

Replacement Chickens: For development of active immunity to coccidiosis

Growing Turkeys: For prevention and control of coccidiosis

Directions

It is suggested that a mixture of Zoamix and some feed ingredient be prepared prior to mixing in with the finished ration. This will ensure thorough and even distribution in the feed.

For chickens grown for meat purposes:

Use 1 lb (454 g) of Zoamix per 2,000 lb (909 kg) of finished product to produce a feed containing 0.0125% zoalene. Zoamix should be thoroughly blended into the finished feed. Feed containing zoalene should be fed continuously as the only ration from the time chicks are placed in floor pens until they are slaughtered for meat.

For replacement chickens:

Feed containing zoalene can be used in a program to raise replacement birds. When used under conditions of exposure to coccidiosis, it will allow immunity to develop adequately to protect against losses due to the disease when the birds are placed on nonmedicated feed for egg laying purposes. The following chart outlines the type of feeding program to follow where complete formulated feed is the sole ration:

 | Starter ration |  |  | Grower ration*
Growing condition | % Zoalene per ton | Zoamix to be added per ton of feed |  | % Zoalene in feed | Zoamix to be added per ton of feed
Growing condition | % Zoalene per ton | (lb) | (g) | % Zoalene in feed | (lb) | (g)
Severe exposure to coccidiosis expected | 0.0125 | 1 | 454 | 0.0083 to 0.0125 | 2/3 to 1 | 303 to 454
Light to moderate exposure to coccidiosis expected | 0.0083 to 0.0125 | 2/3 to 1 | 303 to 454 | 0.004 to 0.0083 | 1/3 to 2/3 | 151 to 303

* Grower ration not to be fed to birds over 14 weeks of age.

For turkeys grown for meat purposes only:

When turkey poults are reared in confinement and severe exposure to coccidiosis is usually a problem, use 1½ lb (681 g) of Zoamix per ton (2,000 lb) of feed to produce a finished feed containing 0.0187% zoalene. Under the usual conditions of rearing turkey poults, or when turkey poults are on range, use 1 lb (454 g) of Zoamix per 2,000 lbs (909 kg) of feed to produce a finished feed containing 0.0125% zoalene. The feed containing zoalene should be fed continuously until the birds are 14 to 16 weeks of age.

Combinations with other drugs

Use only in accordance with the current New Animal Drug Regulation for zoalene, Section 558.680 of the Regulations promulgated under the Federal Food, Drug and Cosmetic Act.

Cautions

Not to be fed to laying birds.

Consult a veterinarian or poultry pathologist if losses exceed 0.5% in a two-day period.

Avoid inhaling dust.

Avoid contact with eyes.

STORAGE AND HANDLING

Store below 37°C

Restricted Drug (California) - use only as directed. Not for human use.
Approved by FDA under NADA # 011-116
zoetis
Manufactured by Zoetis LLC,
Salisbury, MD 21801
Distributed by:
Zoetis Inc.
Kalamazoo, MI 49007
Product of China

Net wt 50 LB (22.68 kg)

40026637